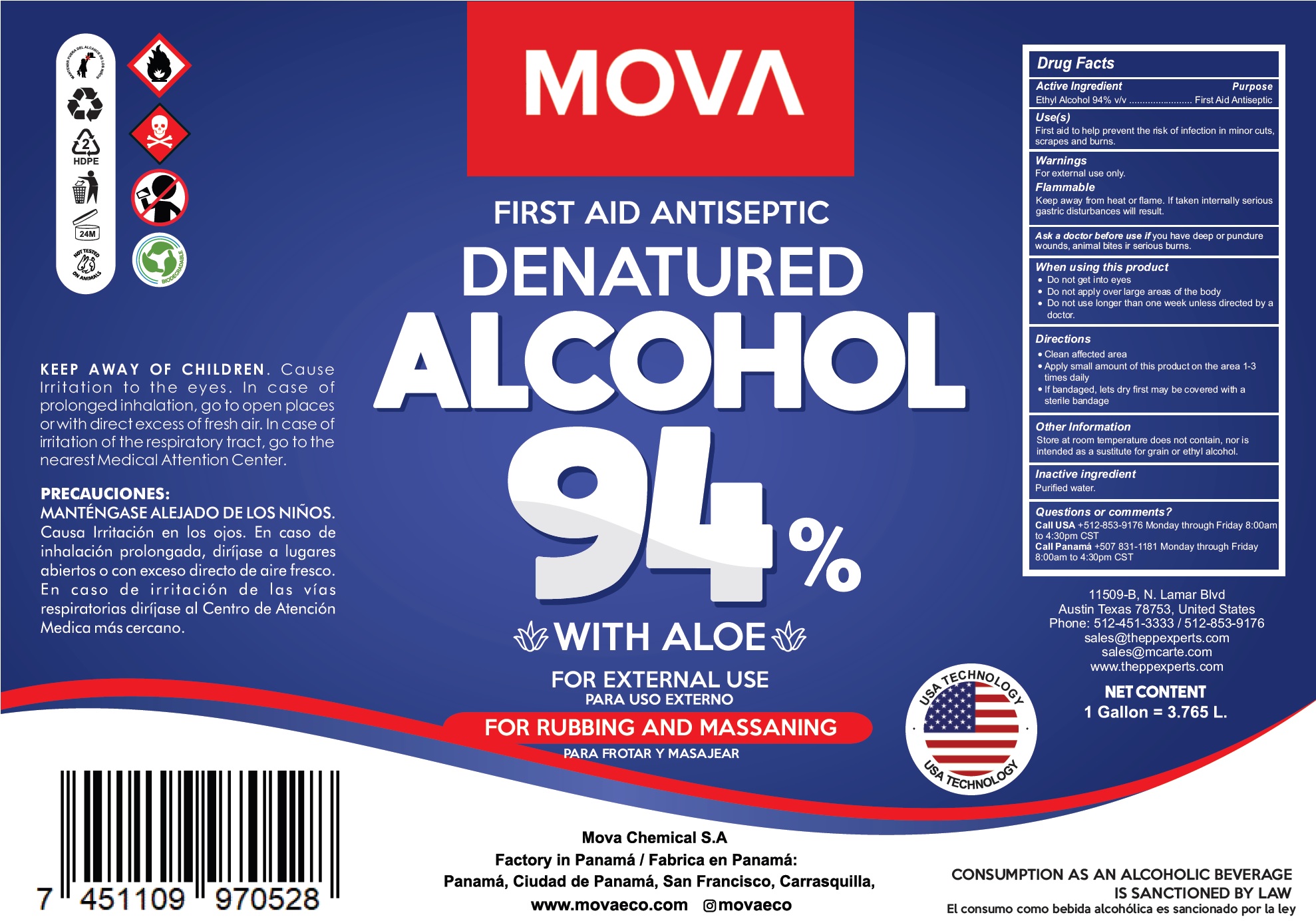 DRUG LABEL: Mova First Aid Antiseptic Denatured Alcohol 94
NDC: 81235-002 | Form: LIQUID
Manufacturer: Mova Chemical S.A
Category: otc | Type: HUMAN OTC DRUG LABEL
Date: 20230104

ACTIVE INGREDIENTS: ALCOHOL 0.94 mL/1 mL
INACTIVE INGREDIENTS: WATER

Mova First aid Antiseptic Denatured Alcohol 94%

Active Ingredient

Ethyl Alcohol 94% v/v

Purpose

First Aid Antiseptic

Use(s)

First aid to help prevent the risk of infection in minor cuts, scrapes and burns.

Warnings

For external use only

Flammable

Keep away from heat or flame. If taken internally serious gastric disturbances will result

Ask a doctor before use if

you have deep or puncture wounds, animal bites ir serious burns.

When using this product

- Do not get into eyes
- Do not apply over large areas of the body

Do not use

- longer than one week unless directed by a doctor.

KEEP AWAY OF CHILDREN.

Cause Irritation to the eyes. In case of prolonged inhalation, go to open places or with direct excess of fresh air. In case of irritation of the respiratory tract, go to the nearest Medical Attention Center.

Directions

- Clean affected area
- Apply small amount of this product on the area 1-3 times daily
- If bandaged, lets dry first may be covered with a sterile bandage

Other Information

Store at room temperature does not contain, nor is intended as a sustitute for grain or ethyl alcohol.

Inactive ingredient

Purified water.

Questions or comments?

Call USA +512-853-9176 Monday through Friday 8:00am to 4:30pm CST
Call Panamá +507 831-1181 Monday through Friday 8:00am to 4:30pm CST